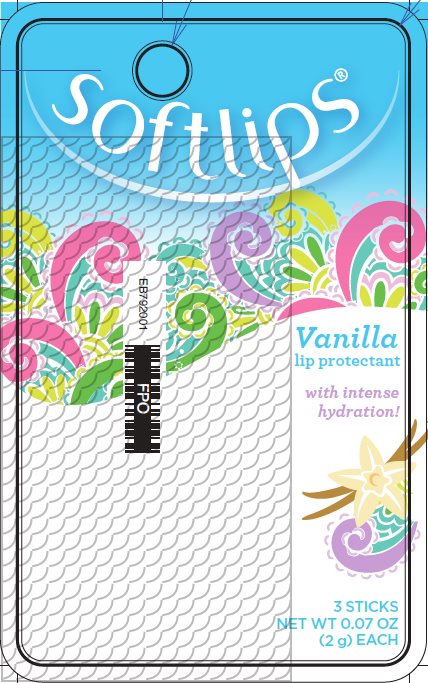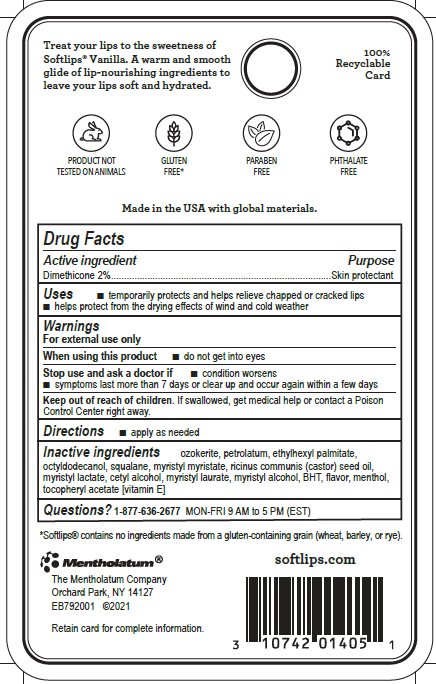 DRUG LABEL: Softlips Vanilla
NDC: 10742-8508 | Form: STICK
Manufacturer: The Mentholatum Company
Category: otc | Type: HUMAN OTC DRUG LABEL
Date: 20241217

ACTIVE INGREDIENTS: DIMETHICONE 20 mg/1 g
INACTIVE INGREDIENTS: CERESIN; PETROLATUM; ETHYLHEXYL PALMITATE; OCTYLDODECANOL; SQUALANE; MYRISTYL MYRISTATE; CASTOR OIL; MYRISTYL LACTATE; CETYL ALCOHOL; MYRISTYL LAURATE; MYRISTYL ALCOHOL; BUTYLATED HYDROXYTOLUENE; MENTHOL, UNSPECIFIED FORM; .ALPHA.-TOCOPHEROL

Drug Facts - Softlips Vanilla

Active ingredient

Dimethicone 2%

Purpose

Dimethicone - Skin protectant

Uses

- temporarily protects and helps relieve chapped or cracked lips
- helps protect from the drying effects of wind and cold weather

Warnings

For external use only

When using this product

- do not get into eyes

Stop use and ask a doctor if

- condition worsens
- symptoms last more than 7 days or clear up and occur again within a few days

Keep out of reach of children.

If swallowed, get medical help or contact a Poison Control Center right away.

Directions

- apply as needed

Inactive ingredients

ozokerite, petrolatum, ethylhexyl palmitate, octyldodecanol, squalane, myristyl myristate, ricinus communis (castor) seed oil, myristyl lactate, cetyl alcohol, myristyl laurate, myristyl alcohol, BHT, flavor, menthol, tocopheryl acetatate [vitamin E]

Questions?

1-877-636-2677 MON-FRI 9AM to 5PM (EST)